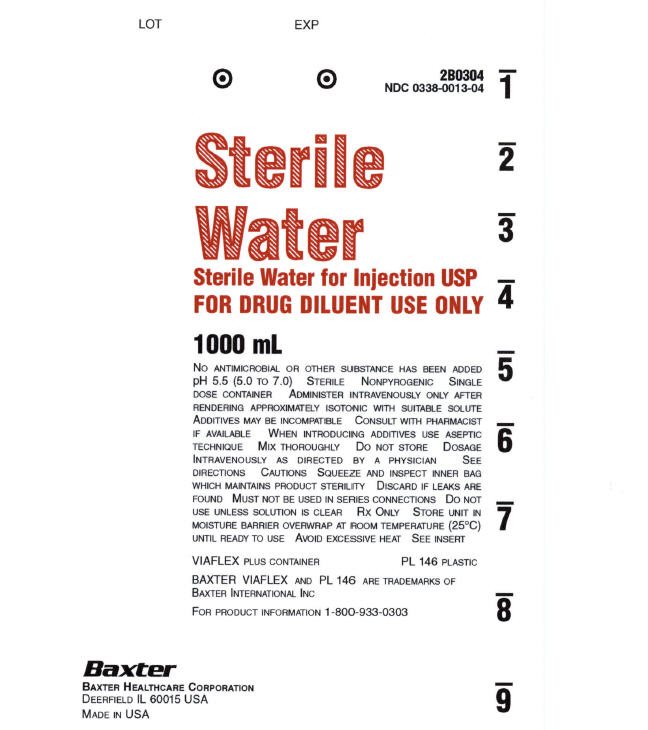 DRUG LABEL: Sterile Water
NDC: 0338-0013 | Form: INJECTION, SOLUTION
Manufacturer: Baxter Healthcare Company
Category: prescription | Type: HUMAN PRESCRIPTION DRUG LABEL
Date: 20191229

ACTIVE INGREDIENTS: WATER 100 mL/100 mL

Sterile Water for Injection, USP
in VIAFLEX Plastic Container
For Drug Diluent Use Only

DESCRIPTION

Sterile Water for Injection, USP, is sterile, nonpyrogenic, distilled water in a single dose container for intravenous administration after addition of a suitable solute. It may also be used as a dispensing container for diluent use. No antimicrobial or other substance has been added. The pH is 5.5 (5.0 to 7.0). The osmolarity is 0.

The VIAFLEX plastic container is fabricated from a specially formulated polyvinyl chloride (PL 146 Plastic). The amount of water that can permeate from inside the container into the overwrap is insufficient to affect the solution significantly. Solutions in contact with the plastic container may leach out certain chemical components from the plastic in very small amounts; however, biological testing was supportive of the safety of the plastic container materials.

CLINICAL PHARMACOLOGY

Sterile Water for Injection, USP is used for fluid replacement only after suitable additives are introduced to approximate isotonicity and to serve as a vehicle for suitable medications.

INDICATIONS AND USAGE

Sterile Water for Injection, USP is indicated in the aseptic preparation of parenteral solutions.

CONTRAINDICATIONS

Sterile Water for Injection, USP is a hemolytic agent due to its hypotonicity. Therefore, it is contraindicated for intravenous administration without additives.

WARNINGS

Do not use for intravenous injection unless adjusted to approximate isotonicity with a suitable solute.

Hemolysis may occur following infusion of Sterile Water for Injection, USP. Hemoglobin induced renal failure has been reported following hemolysis.

PRECAUTIONS

Do not administer unless solution is clear and seal is intact.

ADVERSE REACTIONS

The administration of a suitable admixture of prescribed additives may be associated with adverse reactions because of the solution or the technique of administration including febrile response, infection at the site of injection, venous thrombosis or phlebitis extending from the site of injection, extravasation, and hypervolemia.

If an adverse reaction does occur, discontinue the infusion, evaluate the patient, institute appropriate therapeutic countermeasures, and save the remainder of the fluid for examination if deemed necessary.

DOSAGE AND ADMINISTRATION

Following suitable admixture of prescribed additives, the dosage is usually dependent upon the age, weight and clinical condition of the patient as well as laboratory determinations. See directions accompanying additive drug.

Parenteral drug products should be inspected visually for particulate matter and discoloration prior to administration whenever solution and container permit.

Injections in VIAFLEX plastic containers are intended for intravenous administration using sterile equipment.

Additives may be incompatible. Complete information is not available. Those additives known to be incompatible should not be used. Consult with pharmacist, if available. If, in the informed judgment of the physician, it is deemed advisable to introduce additives, use aseptic technique. Do not store an unused portion of Sterile Water for Injection, USP. Mix thoroughly when additives have been introduced. Do not store solutions containing additives.

HOW SUPPLIED

Sterile Water for Injection, USP is supplied in VIAFLEX plastic containers as follows:

1000 mL | 2B0304 | NDC 0338-0013-04

Exposure of pharmaceutical products to heat should be minimized. Avoid excessive heat. It is recommended the product be stored at room temperature (25°C); brief exposure up to 40°C does not adversely affect the product.

DIRECTIONS FOR USE OF VIAFLEX PLASTIC CONTAINER

Warning: Do not use plastic containers in series connections. Such use could result in air embolism due to residual air being drawn from the primary container before administration of the fluid from the secondary container is completed.

To Open

Tear overwrap down side at slit and remove solution container. Visually inspect the container. If the port outlet protector is damaged, detached, or not present, discard container as solution path sterility may be impaired. Some opacity of the plastic due to moisture absorption during the sterilization process may be observed. This is normal and does not affect the solution quality or safety. The opacity will diminish gradually. Check for minute leaks by squeezing inner bag firmly. If leaks are found, discard solution as sterility may be impaired. See following directions.

Preparation for Administration After Rendering Isotonic

1. Suspend container from eyelet support.
2. Remove plastic protector from outlet port at bottom of container.
3. Attach administration set. Refer to complete directions accompanying set.

Warning: Additives may be incompatible.

To add medication before administration

1. Prepare medication site.
2. Using syringe with 19 to 22 gauge needle, puncture resealable medication port and inject.
3. Mix solution and medication thoroughly. For high density medication such as potassium chloride, squeeze ports while ports are upright and mix thoroughly.

To add medication during administration

1. Close clamp on the set.
2. Prepare medication site.
3. Using syringe with 19 to 22 gauge needle, puncture resealable medication port and inject.
4. Remove container from IV pole and/or turn to an upright position.
5. Evacuate both ports by squeezing them while container is in the upright position.
6. Mix solution and medication thoroughly.
7. Return container to in use position and continue administration.

Baxter Healthcare Corporation

Deerfield, IL 60015 USA

Printed in USA

07 19 73 675

Rev. September 2014

Baxter, Viaflex, and PL 146 are trademarks of Baxter International Inc.

PACKAGE LABEL.PRINCIPLE DISPLAY PANEL

Sterile Water Container Label

Sterile Water Container Label

LOT EXP

2B0304

NDC 0338-0013-04

STERILE WATER

STERILE WATER FOR INJECTION USP

FOR DRUG DILUENT USE ONLY

1000mL

NO ANTIMICROBIAL OR OTHER SUBSTANCE HAS BEEN ADDED

pH 5.5 (5.0 TO 7.0) STERILE NONPYROGENIC SINGLE

DOSE CONTAINER ADMINISTER INTRAVENOUSLY ONLY AFTER

RENDERING APPROXIMATELY ISOTONIC WITH SUITABLE SOLUTE

ADDITIVES MAY BE INCOMPATIBLE CONSULT WITH PHARMACIST

IF AVAILABLE WHEN INTRODUCING ADDITIVES USE ASEPTIC

TECHNIQUE MIX THOROUGHLY DO NO STORE DOSAGE

INTRAVENOUSLY AS DIRECTED BY A PHYSICIAN SEE

DIRECTIONS CAUTIONS SQUEEZE AND INSPECT INNER BAG

WHICH MAINTAINS PRODUCT STERILITY DISCARD IF LEAKS ARE

FOUND MUST NOT BE USED IN SERIES CONNECTIONS DO NOT

USE UNLESS SOLUTION IS CLEAR RX ONLY STORE UNIT IN

MOISTURE BARRIER OVERWRAP AT ROOM TEMPERATURE (25°C)

UNTIL READY TO USE AVOID EXCESSIVE HEAT SEE INSERT

VIAFLEX PLUS CONTAINER PL 146 PLASTIC

BAXTER VIAFLEX AND PL 146 ARE TRADEMARKS OF

BAXTER INTERNATIONAL INC

FOR PRODUCT INFORMATION 1-800-933-0303

BAXTER

BAXTER HEALTHCARE CORPORATION

DEERFIELD IL 60015 USA

MADE IN THE USA